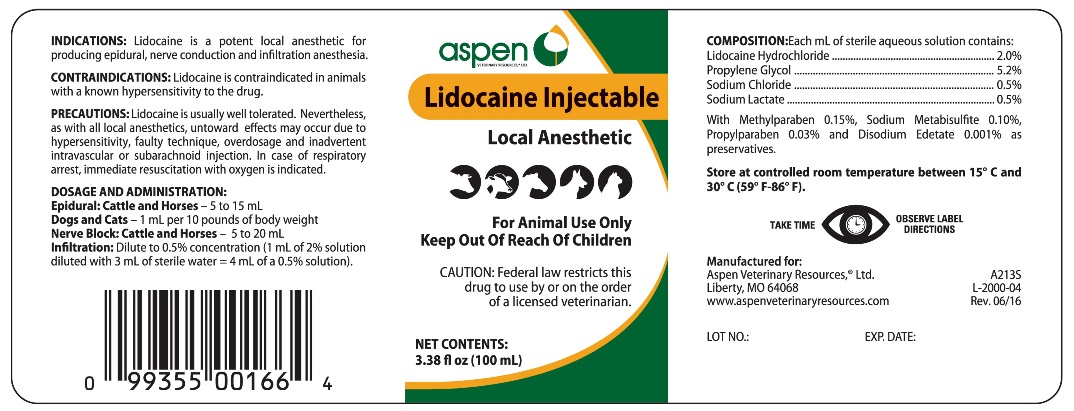 DRUG LABEL: LIDOCAINE 
NDC: 46066-222 | Form: INJECTION
Manufacturer: Aspen Veterinary Resources, Ltd.
Category: animal | Type: PRESCRIPTION ANIMAL DRUG LABEL
Date: 20190531

ACTIVE INGREDIENTS: LIDOCAINE HYDROCHLORIDE 0.02 g/1 mL

LIDOCAINE INJECTION Local Anesthetic

INDICATIONS AND USAGE

CAUTION: Federal law restricts this drug to use by or on the order of a licensed veterinarian.

For Animal Use Only

Keep Out of Reach of Children

INDICATIONS

Lidocaine is a potent local anesthetic producing epidural, nerve conduction and infiltration anesthesia.

CONTRAINDICATIONS

Lidocaine is contraindicated in animals with a known hypersensitivity to the drug.

PRECAUTIONS

Lidocaine is usually well tolerated. Nevertheless, as with all local anesthetics, untoward effects may occur due to hypersensitivity, faulty technique, overdosage and inadvertent intravascular or subarachnoid injection. In case of respiratory arrest, immediate resuscitation with oxygen is indicated.

DOSAGE AND ADMINISTRATION

Epidural
Cattleand Horses - 5 to 15 mL
Dogsand Cats - 1 mL per 10 pounds of body weight.
Nerve Block
Cattleand Horses - 5 to 20 mL
Infiltration
Dilute to 0.5% concentration (1 mL of 2% solution diluted with 3 mL of sterile water = 4 mL of a 0.5% solution)

COMPOSITION

Each mL of sterile aqueous solution contains:
Lidocaine Hydrochloride........................2.0%
Propylene Glycol..................................5.2%
Sodium Chloride...................................0.5%
Sodium Lactate....................................0.5%
with Methylparaben 0.15%, Sodium Metabisulfite 0.10%,
Propylparaben 0.03%, and Disodium Edetate 0.001% as preservatives.

STORAGE AND HANDLING

Store at controlled room temperature between 15oC and 30oC (59oF-86oF).

TAKE TIME OBSERVE LABEL DIRECTIONS